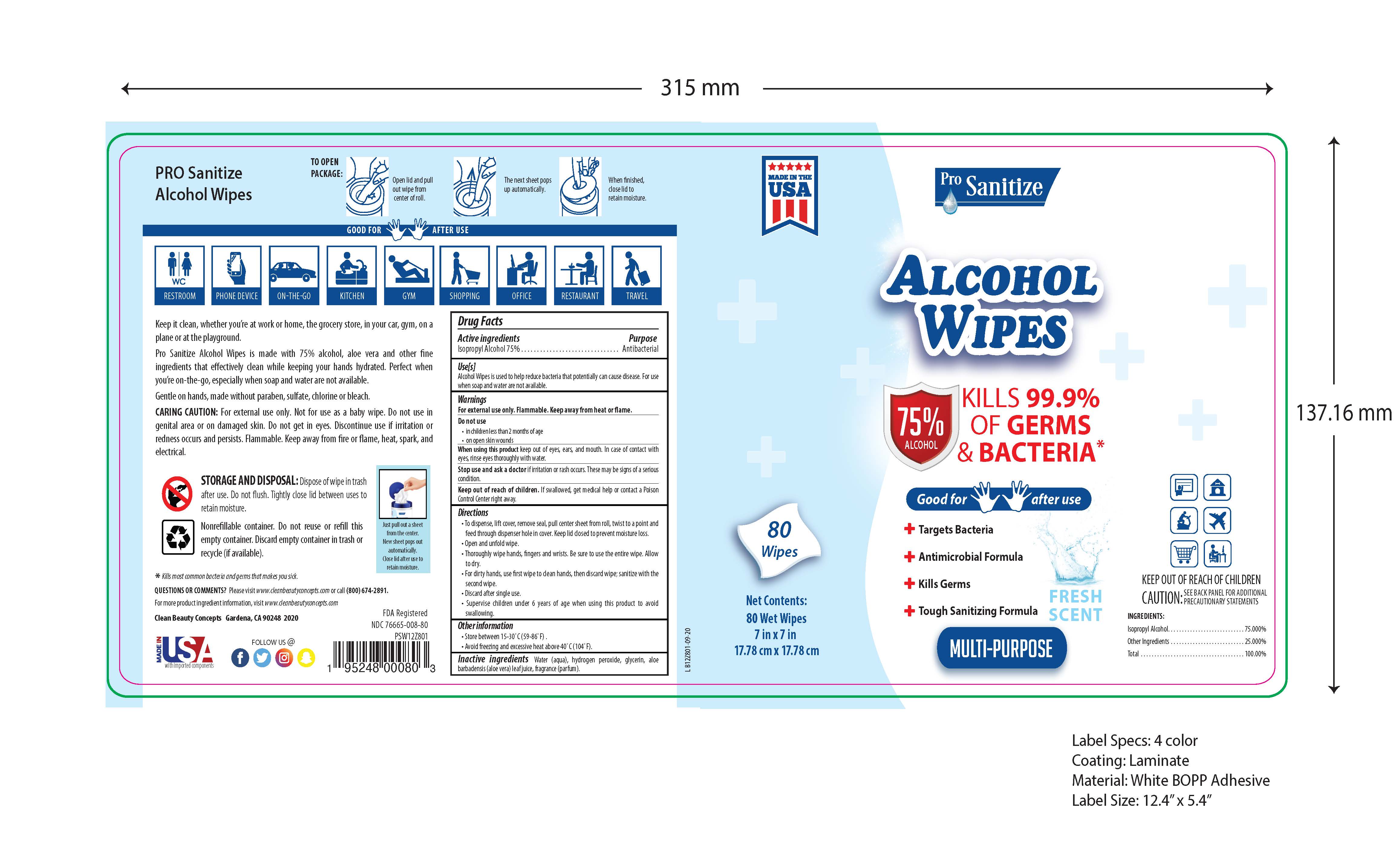 DRUG LABEL: Pro-Sanitize
NDC: 76665-008 | Form: LIQUID
Manufacturer: Clean Beauty Concepts
Category: otc | Type: HUMAN OTC DRUG LABEL
Date: 20201002

ACTIVE INGREDIENTS: ISOPROPYL ALCOHOL 75 mL/100 mL
INACTIVE INGREDIENTS: FRAGRANCE CLEAN ORC0600327 0.3 mL/100 mL; GLYCERIN 1.45 mL/100 mL; HYDROGEN PEROXIDE 0.125 mL/100 mL; WATER 22.825 mL/100 mL; ALOE VERA LEAF 0.3 mL/100 mL

The sanitizer wipes is manufactured using only the following United States Pharmacopoeia (USP) grade ingredients:

1. Alcohol (Isopropyl alcohol) (USP or Food Chemical Codex (FCC) grade) (75%, volume/volume (v/v)) in an aqueous solution denatured according to Alcohol and Tobacco Tax and Trade Bureau regulations in 27 CFR part 20.
2. Glycerol
3. Hydrogen peroxide
4. Sterile distilled water or boiled cold water. (27.465%)
5. Fragrance (Parfum)
6. Aloe vera lead extract

Active Ingredient(s)

Isopropyl Alcohol 75% v/v. Purpose: Antiseptic

Purpose

Antiseptic

Use

Sanitizing alcohol wipes to help reduce bacteria that potentially can cause disease. For use when soap and water are not available

Warnings

For external use only. Flammable. Keep away from heat or flame

Do not use

- in children less than 2 months of age
- on open skin wounds

When using this product keep out of eyes, ears, and mouth. In case of contact with eyes, rinse eyes thoroughly with water.
Stop use and ask a doctor if irritation or rash occurs. These may be signs of a serious condition.
Keep out of reach of children. If swallowed, get medical help or contact a Poison Control Center right away.

Stop use and ask a doctor if irritation or rash occurs. These may be signs of a serious condition.

Keep out of reach of children. If swallowed, get medical help or contact a Poison Control Center right away.

Directions

- To dispense, lift cover, remove seal, pull center sheet from roll, twist to a point and feed through dispenser holde in cover. Keep lid closed to prevent moisture loss.
- Open and unfold wipe
- Thoroughly wipe hands, fingers and wrists. Be sure to use the entire wipe. Allow to dry.
- For dirty hands, use first wipe to clean hands, then discard wipe, sanitize with the second wipe.
- Discard after single use
- Supervise children under 6 years of age when using this product to avoid swallowing

Other information

- Store between 15-30C (59-86F)
- Avoid freezing and excessive heat above 40C (104F)

Inactive ingredients

water(aqua), glycerin, hydrogen peroxide, fragrance(parfum), Aloe Barbadensis

Package Label - Principal Display Panel

80ct NDC: 76665-008-80